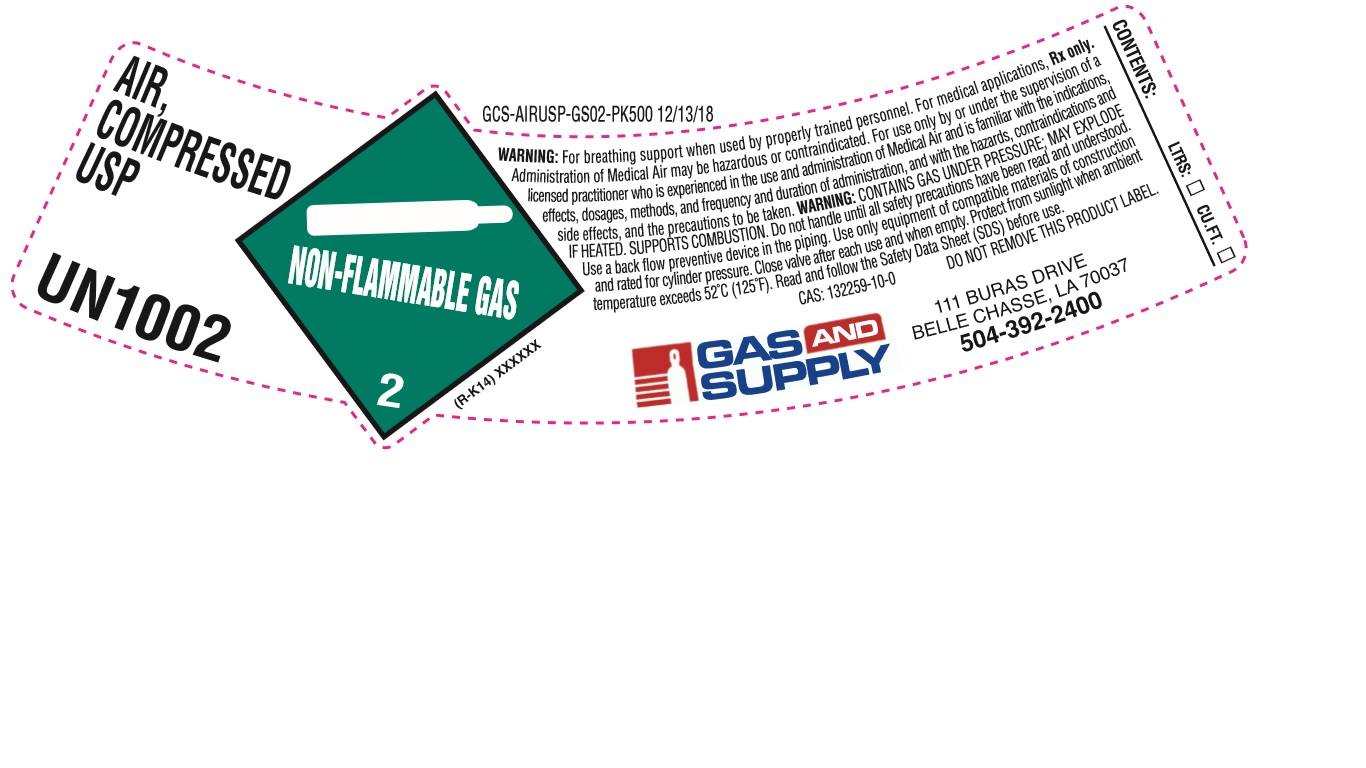 DRUG LABEL: Air
NDC: 42241-003 | Form: GAS
Manufacturer: - INDUSTRIAL WELDING SUPPLY CO. OF HARVEY, INC.
Category: prescription | Type: HUMAN PRESCRIPTION DRUG LABEL
Date: 20251219

ACTIVE INGREDIENTS: OXYGEN 235 mL/1 L

Air

PACKAGE LABEL

AIR, COMPRESSED USP
UN1002
WARNING: For breathing support when used by properly trained personnel. For medical applications, Rx only. Administration of Medical Air may be hazardous or contraindicated. For use only by or under the supervision of a licensed practitioner who is experienced in the use and administration of Medical Air and is familiar with the indications, effects, dosages, methods, and frequency and duration of administration, and with the hazards, contraindications and side effects, and the precautions to be taken. WARNING: CONTAINS GAS UNDER PRESSURE; MAY EXPLODE IF HEATED. SUPPORTS COMBUSTION. Do not handle until all safety precautions have been read and understood. Use a back flow preventive device in the piping. Use only with equipment of compatible materials of construction and rated for cylinder pressure. Close valve after each use and when empty. Protect from sunlight when ambient temperature exceeds 52 C (125 F). Read and follow the Safety Data Sheet (SDS) before use.
CAS: 132259-10-0 DO NOT REMOVE THIS PRODUCT LABEL.
GAS AND SUPPLY
111 BURAS DRIVE
BELLE CHASSE, LA 70037
504-392-2400
CONTENTS: LTRS: CU.F.T.